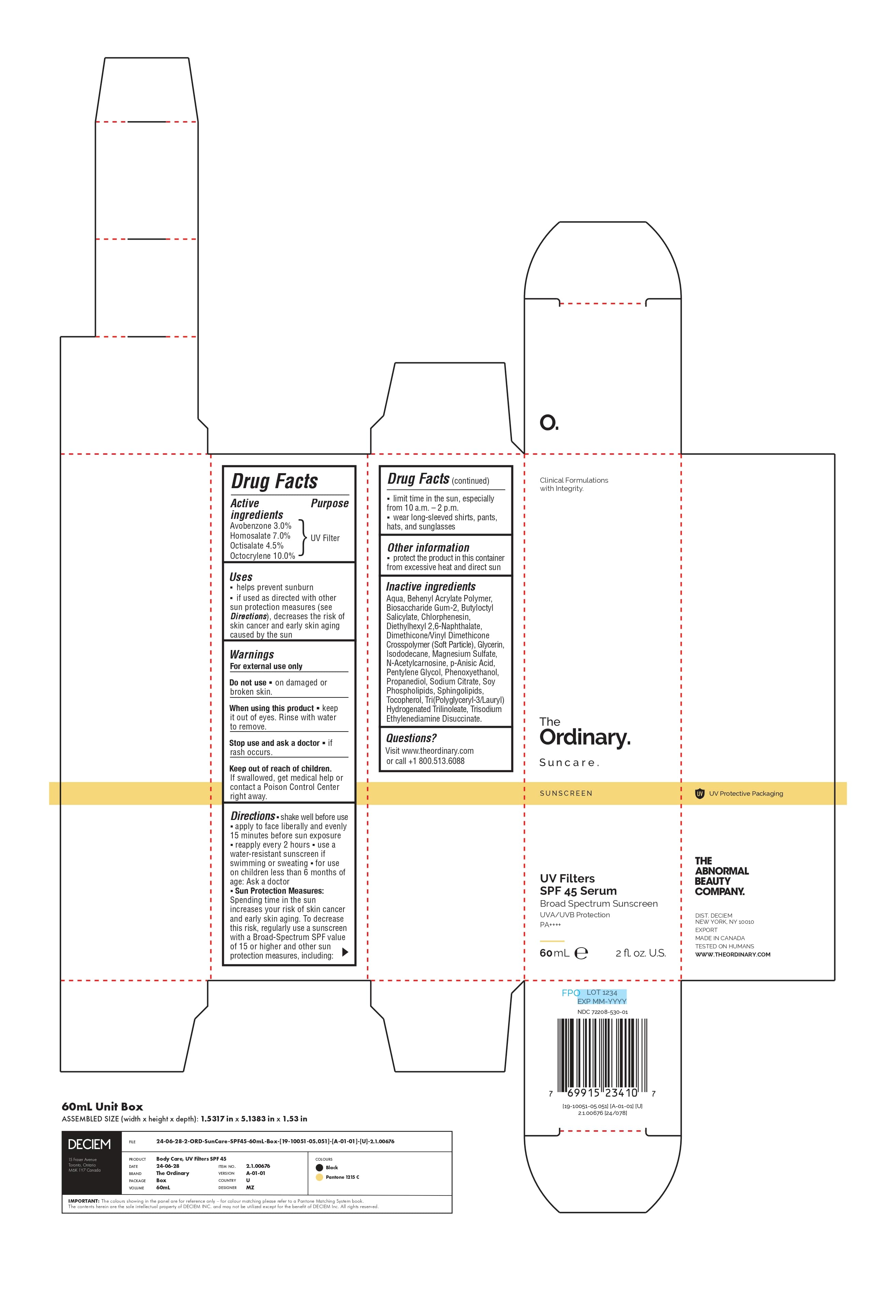 DRUG LABEL: The Ordinary UV Filters SPF 45 Serum
NDC: 72208-530 | Form: EMULSION
Manufacturer: Deciem
Category: otc | Type: HUMAN OTC DRUG LABEL
Date: 20250423

ACTIVE INGREDIENTS: OCTOCRYLENE 100 mg/1 mL; OCTISALATE 45 mg/1 mL; HOMOSALATE 70 mg/1 mL; AVOBENZONE 30 mg/1 mL
INACTIVE INGREDIENTS: SODIUM CITRATE; ISODODECANE; P-ANISIC ACID; TRI(POLYGLYCERYL-3/LAURYL) HYDROGENATED TRILINOLEATE; CHLORPHENESIN; DIMETHICONE/VINYL DIMETHICONE CROSSPOLYMER (SOFT PARTICLE); GLYCERIN; PHENOXYETHANOL; DIETHYLHEXYL 2,6-NAPHTHALATE; BEHENYL ACRYLATE POLYMER; BIOSACCHARIDE GUM-2; BUTYLOCTYL SALICYLATE; MAGNESIUM SULFATE; N-ACETYLCARNOSINE; PENTYLENE GLYCOL; PROPANEDIOL; TRISODIUM ETHYLENEDIAMINE DISUCCINATE; TOCOPHEROL; SOYBEAN LECITHIN; AQUA

ACTIVE INGREDIENT

Avobenzone 3.0%............UV Filter

Homosalate 7.0%.............UV Filter

Octisalate 4.5%................UV Filter

Octocrylene 10.0%...........UV Filter

Keep out of reach of children

Warnings

For External use only

- Do not use on damaged or broken skin
- When using this product. Keep it out of eyes. Rinse with water to remove
- Stop use and ask a doctor if rash occurs
- Keep out of reach of children. If swallowed, get medical help or contact a Poison Control Center right away

Directions

- Shake well before use.
- Apply to face liberally and evenly15 minutes before sun exposure reapply every 2 hours.
- use a water-resistant sunscreen if swimming or sweating.
- for use on children less than 6 months of age: Ask a doctor.
- Sun Protection Measures: Spending time in the sun increases your risk of skin cancer and early skin aging. To decrease this risk, regularly use a sunscreen with a Broad-Spectrum SPF value of 15 or higher and other sun protection measures, including: limit time in the sun, especially from 10 a.m. – 2 p.m. wear long-sleeved shirts, pants, hats, and sunglasses

Questions?

Visit www.theordinary.com

or call +1 800.513.6088

Inactive Ingredients

Aqua, Behenyl Acrylate Polymer, Biosaccharide Gum-2, Butyloctyl Salicylate, Chlorphenesin, Diethylhexyl 2,6-Naphthalate, Dimethicone/Vinyl Dimethicone Crosspolymer (Soft Particle), Glycerin, Isododecane, Magnesium Sulfate, N-Acetylcarnosine, p-Anisic Acid, Pentylene Glycol, Phenoxyethanol, Propanediol, Sodium Citrate, Soy Phospholipids, Tocopherol, Tri(Polyglyceryl-3/Lauryl)Hydrogenated Trilinoleate, Trisodium Ethylenediamine Disuccinate.

Uses

- helps prevent sunburn
- if used as directed with other sun protection measures (see Directions), decreases the risk of skin cancer and early skin aging caused by the sun